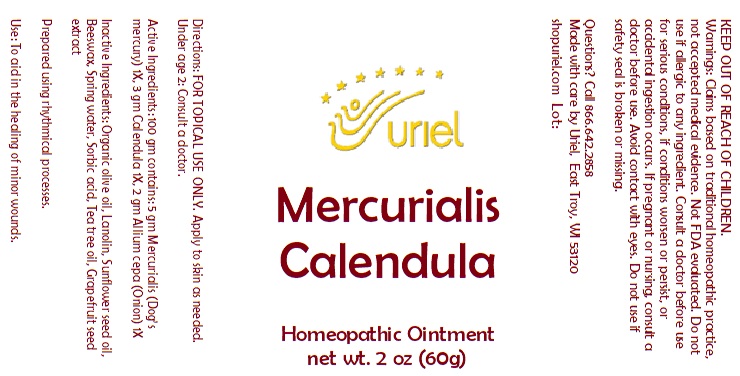 DRUG LABEL: Mercurialis Calendula
NDC: 48951-7192 | Form: OINTMENT
Manufacturer: Uriel Pharmacy Inc.
Category: homeopathic | Type: HUMAN OTC DRUG LABEL
Date: 20251119

ACTIVE INGREDIENTS: MERCURIALIS PERENNIS 1 [hp_X]/1 g; CALENDULA OFFICINALIS FLOWERING TOP 1 [hp_X]/1 g; ONION 1 [hp_X]/1 g
INACTIVE INGREDIENTS: SORBIC ACID; LANOLIN; YELLOW WAX; SUNFLOWER OIL; WATER; CITRUS PARADISI SEED; TEA TREE OIL

Mercurialis Calendula

INDICATIONS AND USAGE

Directions: FOR TOPICAL USE ONLY.

DOSAGE AND ADMINISTRATION

Apply to skin as needed. Under age 2: Consult a doctor.

ACTIVE INGREDIENT

Active Ingredients: 100 gm contains: 50 gm Mercurialis (Dog’s mercury) 1X, 30 gm Calendula 1X, 20 gm Allium cepa (Onion) 1X

INACTIVE INGREDIENT

Inactive Ingredients: Lanolin, Beeswax, Sunflower seed oil, Spring water, Sorbic acid, Tea tree oil, Grapefruit seed extract

prepared using rhythmical processes

PURPOSE

Use: To aid in the healing of minor wounds.

KEEP OUT OF REACH OF CHILDREN.

WARNINGS

Warnings: Claims based on traditional homeopathic practice, not accepted medical evidence. Not FDA evaluated. Do not use if allergic to any ingredient. Consult a doctor before use for serious conditions, if conditions worsen or persist, or accidental ingestion occurs. If pregnant or nursing, consult a doctor before use. Avoid contact with eyes. Do not use if safety seal is broken or missing.

Questions? Call 866.642.2858
Made with care by Uriel,East Troy,WI 53120
shopuriel.com Lot: